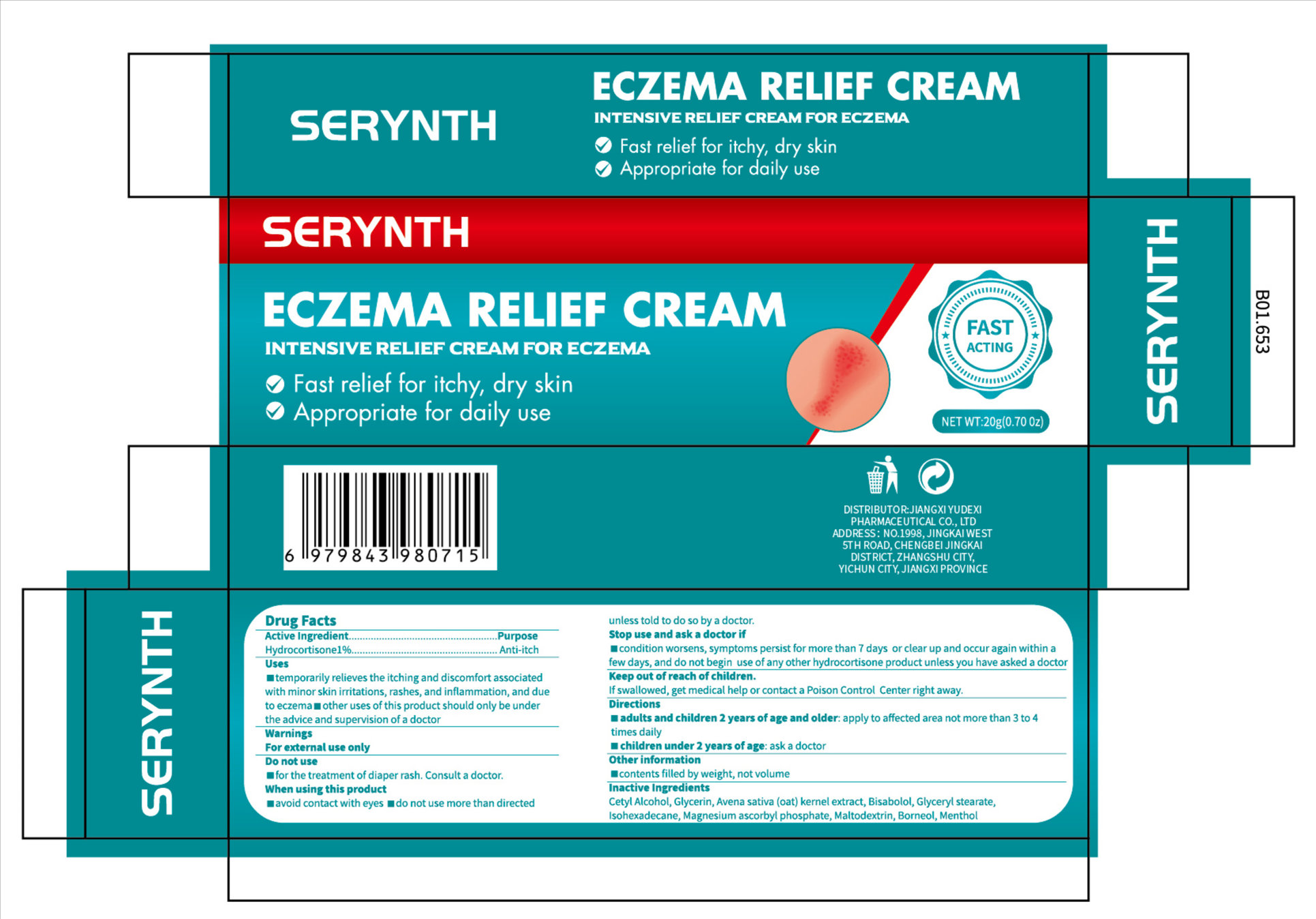 DRUG LABEL: SERYNTH ECZEMA RELIEF
NDC: 85248-104 | Form: CREAM
Manufacturer: Jiangxi Yudexi Pharmaceutical Co., LTD
Category: otc | Type: HUMAN OTC DRUG LABEL
Date: 20260208

ACTIVE INGREDIENTS: HYDROCORTISONE 1 g/100 g
INACTIVE INGREDIENTS: GLYCERIN; BISABOLOL; GLYCERYL 1-STEARATE; MAGNESIUM ASCORBYL PHOSPHATE; MENTHOL; OAT; ISOHEXADECANE; MALTODEXTRIN; BORNEOL

85248-104

Active Ingredient

Hydrocortisone 1%

Purpose

Anti-itch

Use

■temporarily relieves the itching and discomfort associated with minor skin irritations,rashes,and inflammation，and due to eczema.■other uses of this product should only be under the advice and supervision of a doctor

Warnings

For external use only

Do not use

■for the treatment of diaper rash. Consult a doctor.

When Using

■avoid contact with eyes ■do not use more than directed unless told to do so by a doctor

Stop Use

■condition worsens, symptoms persist for more than 7 days or clear up and occur again within a few days, and do not begin use of any other hydrocortisone product unless you have asked a doctor

Ask Doctor

■condition worsens, symptoms persist for more than 7 days or clear up and occur again within a few days, and do not begin use of any other hydrocortisone product unless you have asked a doctor

Keep Oot Of Reach Of Children

If swallowed, get medical help or contact a Poison Control Center right away

Directions

■adults and children 2 years of age and older: apply to affected area not
more than 3 to 4 times daily
■children under 2 years of age: ask a doctor

Other information

■contents filled by weight, not volume

Inactive ingredients

Cetyl Alcohol, Glycerin, Avena sativa (oat) kernel extract, Bisabolol, Glyceryl
stearate,Isohexadecane,Magnesium ascorbyl phosphate. Maltodextrin.Borneol. Menthol